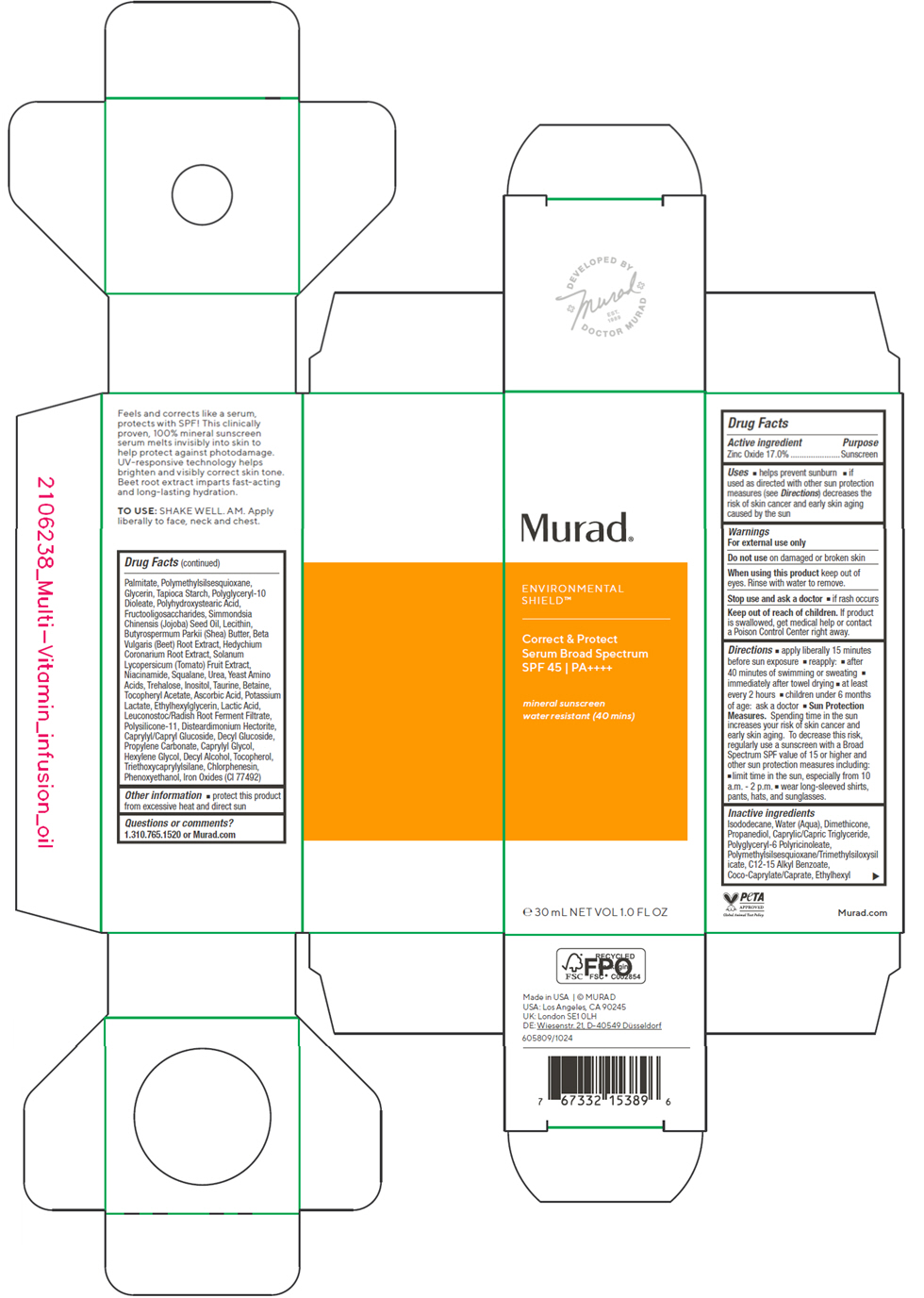 DRUG LABEL: Correct and Protect Serum Broad Spectrum
NDC: 70381-135 | Form: LOTION
Manufacturer: Murad, LLC
Category: otc | Type: HUMAN OTC DRUG LABEL
Date: 20250619

ACTIVE INGREDIENTS: ZINC OXIDE 17 g/100 mL
INACTIVE INGREDIENTS: ISODODECANE; WATER; DIMETHICONE; PROPANEDIOL; MEDIUM-CHAIN TRIGLYCERIDES; POLYGLYCERYL-6 POLYRICINOLEATE; POLYMETHYLSILSESQUIOXANE/TRIMETHYLSILOXYSILICATE; ALKYL (C12-15) BENZOATE; COCOYL CAPRYLOCAPRATE; ETHYLHEXYL PALMITATE; POLYMETHYLSILSESQUIOXANE (4.5 MICRONS); GLYCERIN; STARCH, TAPIOCA; POLYGLYCERYL-10 DIOLEATE; POLYHYDROXYSTEARIC ACID (2300 MW); BETA VULGARIS ROOT FRUCTOOLIGOSACCHARIDES; JOJOBA OIL; SOYBEAN LECITHIN; SHEA BUTTER; BEET; HEDYCHIUM CORONARIUM ROOT; TOMATO; NIACINAMIDE; SQUALANE; UREA; AMINO ACIDS, SOURCE UNSPECIFIED; TREHALOSE; TAURINE; INOSITOL; BETAINE; .ALPHA.-TOCOPHEROL ACETATE; TOCOPHEROL; ASCORBIC ACID; POTASSIUM LACTATE; ETHYLHEXYLGLYCERIN; LACTIC ACID, UNSPECIFIED FORM; LEUCONOSTOC/RADISH ROOT FERMENT FILTRATE; DIMETHICONE/VINYL DIMETHICONE CROSSPOLYMER (SOFT PARTICLE); DISTEARDIMONIUM HECTORITE; CAPRYLYL/CAPRYL OLIGOGLUCOSIDE; DECYL GLUCOSIDE; DECYL ALCOHOL; PROPYLENE CARBONATE; CAPRYLYL GLYCOL; HEXYLENE GLYCOL; TRIETHOXYCAPRYLYLSILANE; CHLORPHENESIN; PHENOXYETHANOL; FERRIC OXIDE YELLOW

Correct & Protect Serum Broad Spectrum
SPF 45

Drug Facts

Active ingredient

Zinc Oxide 17.0%

Purpose

Sunscreen

Uses

- helps prevent sunburn
- if used as directed with other sun protection measures (see Directions) decreases the risk of skin cancer and early skin aging caused by the sun

Warnings

For external use only

Do not use on damaged or broken skin

When using this product keep out of eyes. Rinse with water to remove.

Stop use and ask a doctor

- if rash occurs

Keep out of reach of children. If product is swallowed, get medical help or contact a Poison Control Center right away.

Directions

- apply liberally 15 minutes before sun exposure
- reapply:
  - after 40 minutes of swimming or sweating
  - immediately after towel drying
  - at least every 2 hours
- children under 6 months of age: ask a doctor
- Sun Protection Measures. Spending time in the sun increases your risk of skin cancer and early skin aging. To decrease this risk, regularly use a sunscreen with a Broad Spectrum SPF value of 15 or higher and other sun protection measures including:
  - limit time in the sun, especially from 10 a.m. - 2 p.m.
  - wear long-sleeved shirts, pants, hats, and sunglasses.

Inactive ingredients

Isododecane, Water (Aqua), Dimethicone, Propanediol, Caprylic/Capric Triglyceride, Polyglyceryl-6 Polyricinoleate, Polymethylsilsesquioxane/Trimethylsiloxysilicate, C12-15 Alkyl Benzoate, Coco-Caprylate/Caprate, Ethylhexyl Palmitate, Polymethylsilsesquioxane, Glycerin, Tapioca Starch, Polyglyceryl-10 Dioleate, Polyhydroxystearic Acid, Fructooligosaccharides, Simmondsia Chinensis (Jojoba) Seed Oil, Lecithin, Butyrospermum Parkii (Shea) Butter, Beta Vulgaris (Beet) Root Extract, Hedychium Coronarium Root Extract, Solanum Lycopersicum (Tomato) Fruit Extract, Niacinamide, Squalane, Urea, Yeast Amino Acids, Trehalose, Taurine, Inositol, Betaine, Tocopheryl Acetate, Tocopherol, Ascorbic Acid, Potassium Lactate, Ethylhexylglycerin, Lactic Acid, Leuconostoc/Radish Root Ferment Filtrate, Polysilicone-11, Disteardimonium Hectorite, Caprylyl/Capryl Glucoside, Decyl Glucoside, Decyl Alcohol, Propylene Carbonate, Caprylyl Glycol, Hexylene Glycol, Triethoxycaprylylsilane, Chlorphenesin, Phenoxyethanol, Iron Oxides (CI 77492)

Other information

- protect this product from excessive heat and direct sun

Questions or comments?

1.310.765.1520 or Murad.com

PRINCIPAL DISPLAY PANEL - 30 mL Bottle Carton

Murad®

ENVIRONMENTAL
SHIELD™

Correct & Protect
Serum Broad Spectrum
SPF 45 | PA++++

mineral sunscreen
water resistant (40 mins)

℮ 30 mL NET VOL 1.0 FL OZ